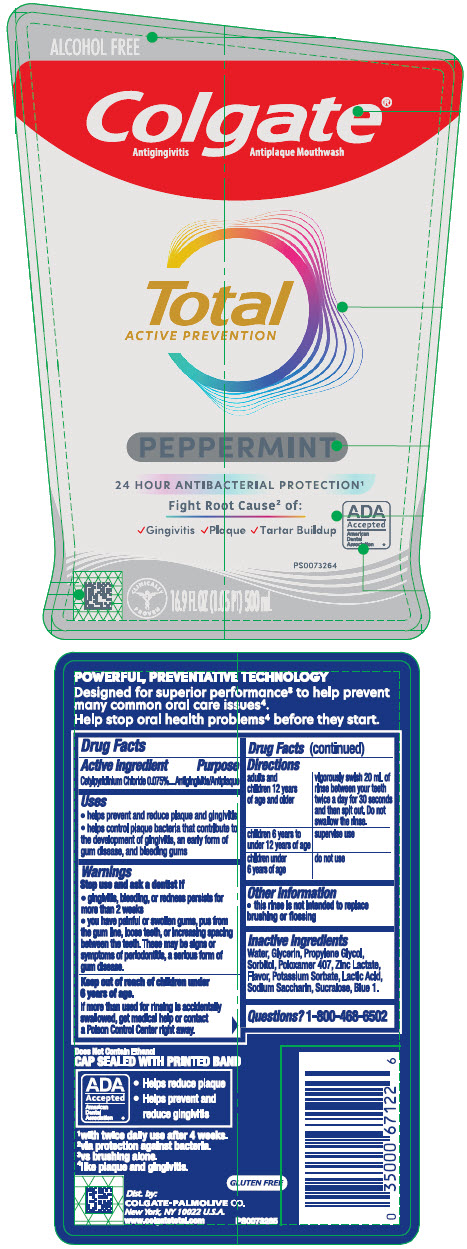 DRUG LABEL: Colgate Total Active Prevention Peppermint
NDC: 35000-279 | Form: RINSE
Manufacturer: COLGATE PALMOLIVE COMPANY
Category: otc | Type: HUMAN OTC DRUG LABEL
Date: 20250804

ACTIVE INGREDIENTS: CETYLPYRIDINIUM CHLORIDE 15 mg/20 mL
INACTIVE INGREDIENTS: WATER; GLYCERIN; PROPYLENE GLYCOL; SORBITOL; POLOXAMER 407; ZINC LACTATE; POTASSIUM SORBATE; LACTIC ACID, UNSPECIFIED FORM; SACCHARIN SODIUM; SUCRALOSE; FD&C BLUE NO. 1

Colgate® Total Active Prevention Peppermint

Drug Facts

Active ingredient

Cetylpyridinium Chloride 0.075%

Purpose

Antigingivitis/Antiplaque

Uses

- helps prevent and reduce plaque and gingivitis
- helps control plaque bacteria that contribute to the development of gingivitis, an early form of gum disease, and bleeding gums

Warnings

Stop use and ask a dentist if

- gingivitis, bleeding, or redness persists for more than 2 weeks
- you have painful or swollen gums, pus from the gum line, loose teeth, or increasing spacing between the teeth. These may be signs or symptoms of periodontitis, a serious form of gum disease.

Keep out of reach of children under 6 years of age.

If more than used for rinsing is accidentally swallowed, get medical help or contact a Poison Control Center right away.

Directions

adults and children 12 years of age and older | vigorously swish 20 mL of rinse between your teeth twice a day for 30 seconds and then spit out. Do not swallow the rinse.
children 6 years to under 12 years of age | supervise use
children under 6 years of age | do not use

Other information

- this rinse is not intended to replace brushing or flossing

Inactive ingredients

Water, Glycerin, Propylene Glycol, Sorbitol, Poloxamer 407, Zinc Lactate, Flavor, Potassium Sorbate, Lactic Acid, Sodium Saccharin, Sucralose, Blue 1.

Questions?

1-800-468-6502

Dist. by:
COLGATE-PALMOLIVE CO.
New York, NY 10022 U.S.A.

PRINCIPAL DISPLAY PANEL - 500 mL Bottle Label

ALCOHOL FREE

Colgate®
Antigingivitis Antiplaque Mouthwash

Total
ACTIVE PREVENTION

PEPPERMINT

24 HOUR ANTIBACTERIAL PROTECTION^1

Fight Root Cause^2 of:

✓Gingivitis ✓Plaque ✓Tartar Buildup

ADA
Accepted
American
Dental
Association ®

CLINICALLY
PROVEN

16.9 FL OZ (1.05 PT) 500 mL

PS0073264